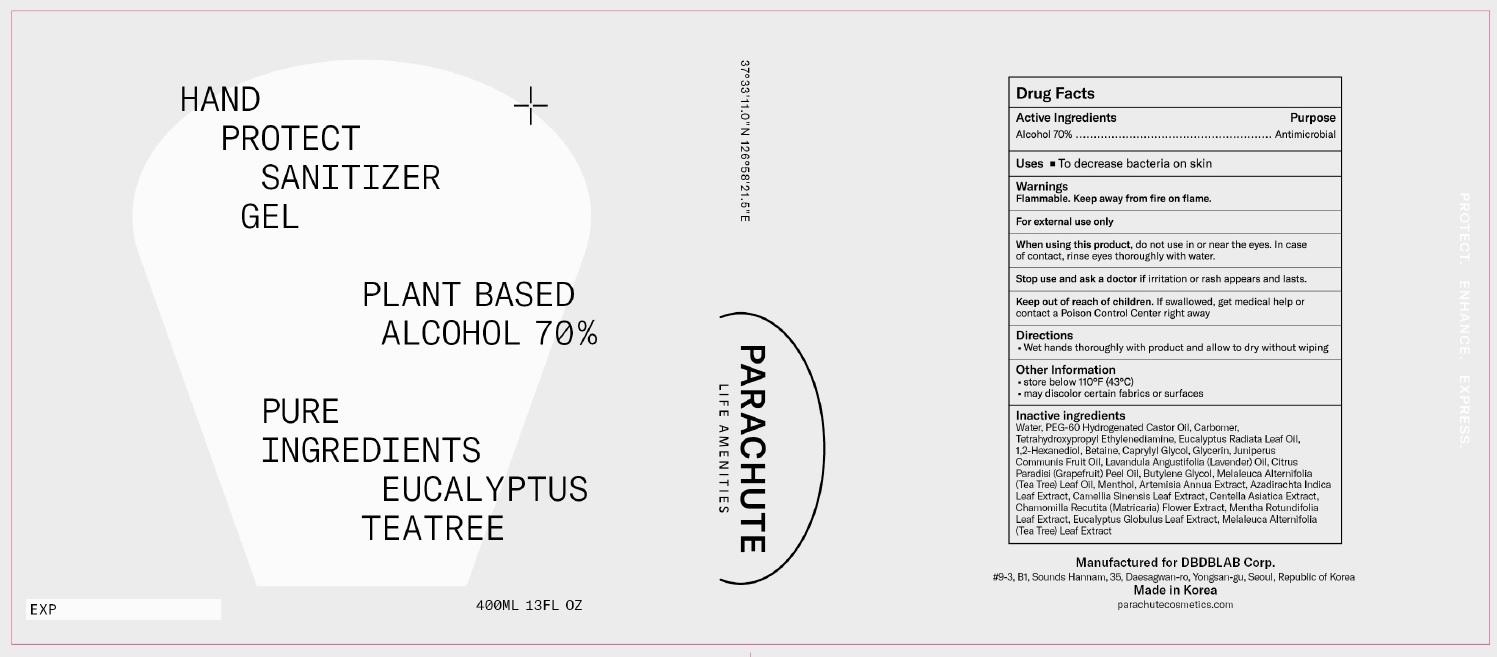 DRUG LABEL: Parachute Hand Protect gel
NDC: 81135-001 | Form: GEL
Manufacturer: DBDBLAB corp.
Category: otc | Type: HUMAN OTC DRUG LABEL
Date: 20210118

ACTIVE INGREDIENTS: ALCOHOL 0.7 mL/1 mL
INACTIVE INGREDIENTS: WATER; PEG-60 HYDROGENATED CASTOR OIL; CARBOMER HOMOPOLYMER, UNSPECIFIED TYPE; EDETOL; EUCALYPTUS OIL; 1,2-HEXANEDIOL; BETAINE; CAPRYLYL GLYCOL; GLYCERIN; JUNIPER BERRY OIL; GRAPEFRUIT OIL; BUTYLENE GLYCOL; LAVENDER OIL; TEA TREE OIL; MENTHOL, UNSPECIFIED FORM; AZADIRACHTA INDICA LEAF; GREEN TEA LEAF; CENTELLA ASIATICA WHOLE; CHAMOMILE; MENTHA SUAVEOLENS LEAF; EUCALYPTUS GLOBULUS LEAF; MELALEUCA ALTERNIFOLIA LEAF

81135-001_Parachute Hand Protect Gel

Active ingredient

Ethyl alcohol 70%

Purpose

Antimicrobial

Use

To decrease bacteria on the skin

Warnings

Flammable. Keep away from fire or flame.

For external use only

When using this product do not use in or near the eyes. In case of contact, rinse eyes thoroughly with water

Stop use and ask a doctor if irritation or rash appears and lasts

Keep out of reach of children. If swallowed, get medical help or contact a Poison Control Center right away.

Directions

- Wet hands thoroughly with product and allow to dry without wiping

Inactive Ingredients:

Water, PEG-60 Hydrogenated Castor Oil, Carbomer, Tetrahydroxypropyl Ethylenediamine, Eucalyptus Radiata Leaf Oil, 1,2-Hexanediol, Betaine, Caprylyl Glycol, Glycerin, Juniperus Communis Fruit Oil, Lavandula Angustifolia (Lavender) Oil, Citrus Paradisi (Grapefruit) Peel Oil, Butylene Glycol, Melaleuca Alternifolia (Tea Tree) Leaf Oil, Menthol, Artemisia Annua Extract, Azadirachta Indica Leaf Extract, Camellia Sinensis Leaf Extract, Centella Asiatica Extract, Chamomilla Recutita (Matricaria) Flower Extract, Mentha Rotundifolia Leaf Extract, Eucalyptus Globulus Leaf Extract, Melaleuca Alternifolia (Tea Tree) Leaf Extract